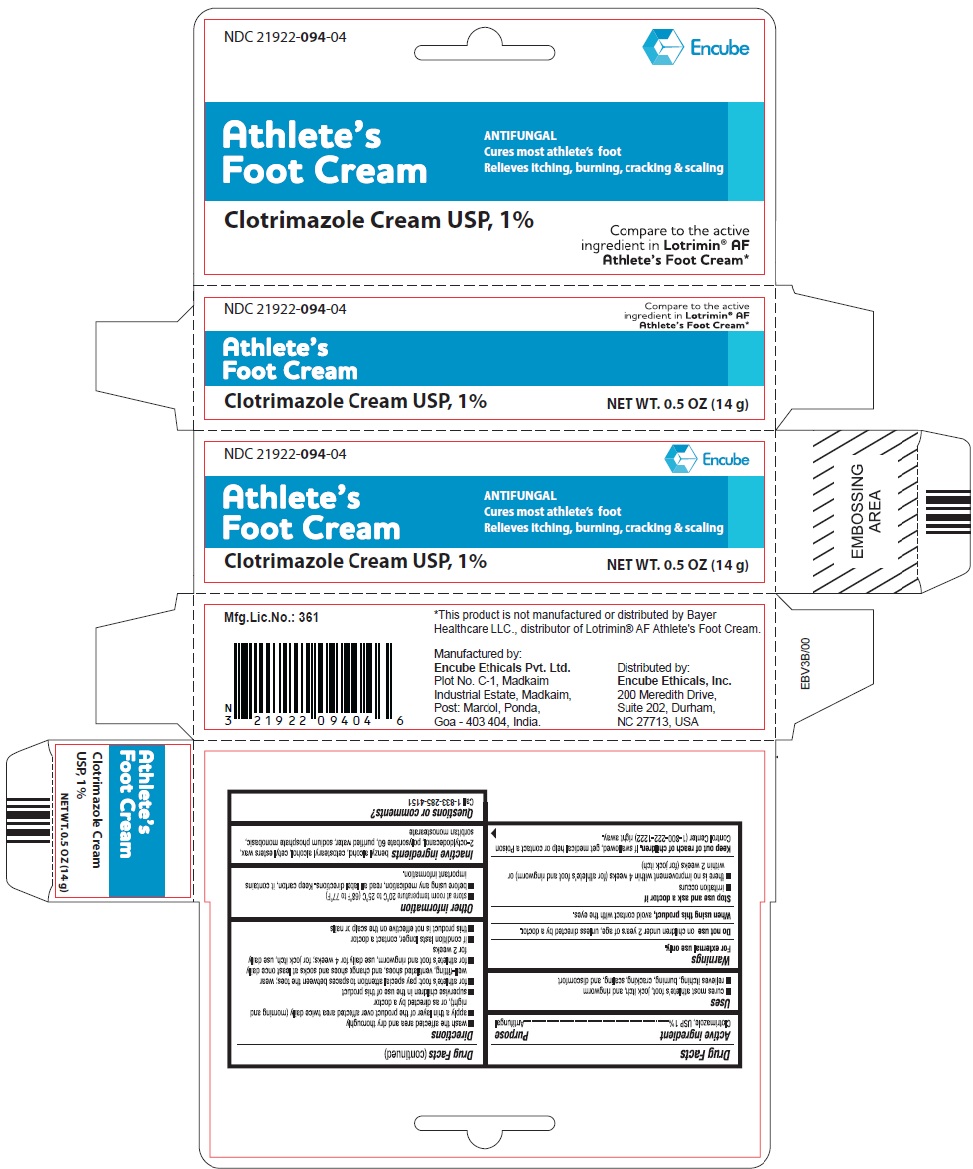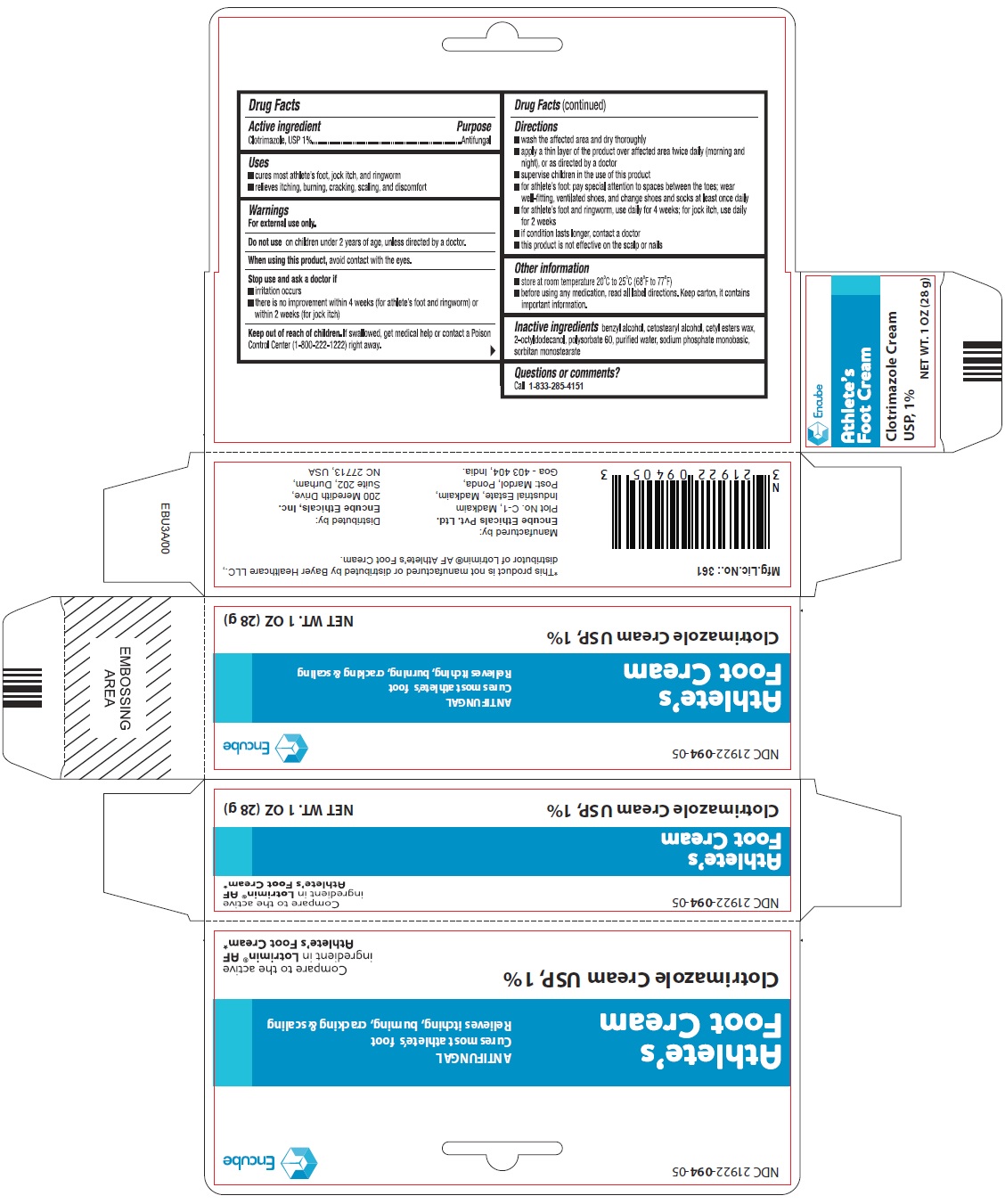 DRUG LABEL: ANTIFUNGAL
NDC: 21922-094 | Form: CREAM
Manufacturer: Encube Ethicals, Inc.
Category: otc | Type: HUMAN OTC DRUG LABEL
Date: 20250904

ACTIVE INGREDIENTS: CLOTRIMAZOLE 10 mg/1 g
INACTIVE INGREDIENTS: BENZYL ALCOHOL; CETOSTEARYL ALCOHOL; OCTYLDODECANOL; POLYSORBATE 60; WATER; SODIUM PHOSPHATE, MONOBASIC; SORBITAN MONOSTEARATE; CETYL ESTERS WAX

Clotrimazole Cream-Antifungal

ACTIVE INGREDIENT(S)

Clotrimazole, USP 1%

PURPOSE

Antifungal

USE(S)

- cures most athlete's foot, jock itch, and ringworm
- relieves itching, burning, cracking, scaling, and discomfort

WARNINGS

For external use only.

DO NOT USE

on children under 2 years of age, unless directed by a doctor.

WHEN USING THIS PRODUCT

avoid contact with the eyes.

STOP USE AND ASK DOCTOR IF

- irritation occurs
- there is no improvement within 4 weeks (for athlete's foot and ringworm) or within 2 weeks (for jock itch)

KEEP OUT OF REACH OF CHILDREN

If swallowed, get medical help or contact a Poison Control Center (1-800-222-1222) right away.

DIRECTIONS

- wash the affected area and dry thoroughly
- apply a thin layer of the product over affected area twice daily (morning and night), or as directed by a doctor
- supervise children in the use of this product
- for athlete's foot: pay special attention to spaces between the toes; wear well-fitting, ventilated shoes, and change shoes and socks at least once daily
- for athlete's foot and ringworm, use daily for 4 weeks; for jock itch, use daily for 2 weeks
- if condition lasts longer, contact a doctor
- this product is not effective on the scalp or nails

OTHER INFORMATION

- store at room temperature 20°C to 25°C (68°F to 77°F)
- before using any medication, read all label directions. Keep carton, It contains important information.

INACTIVE INGREDIENTS

benzyl alcohol, cetostearyl alcohol, cetyl esters wax, 2-octyldodecanol, polysorbate 60, purified water, sodium phosphate monobasic, sorbitan monostearate

QUESTIONS OR COMMENTS?

Call 1-833-285-4151

PRINCIPAL DISPLAY PANEL

Athlete's Foot Cream

Clotrimazole Cream USP, 1% (Antifungal)

NET WT. 0.5 OZ (14 g)

Athlete's Foot Cream

Clotrimazole Cream USP, 1% (Antifungal)

NET WT. 1 OZ (28 g)